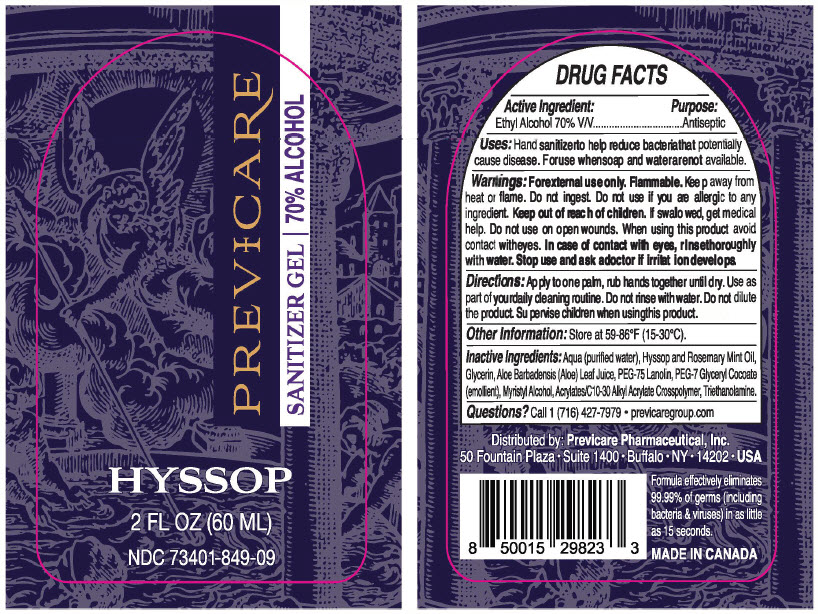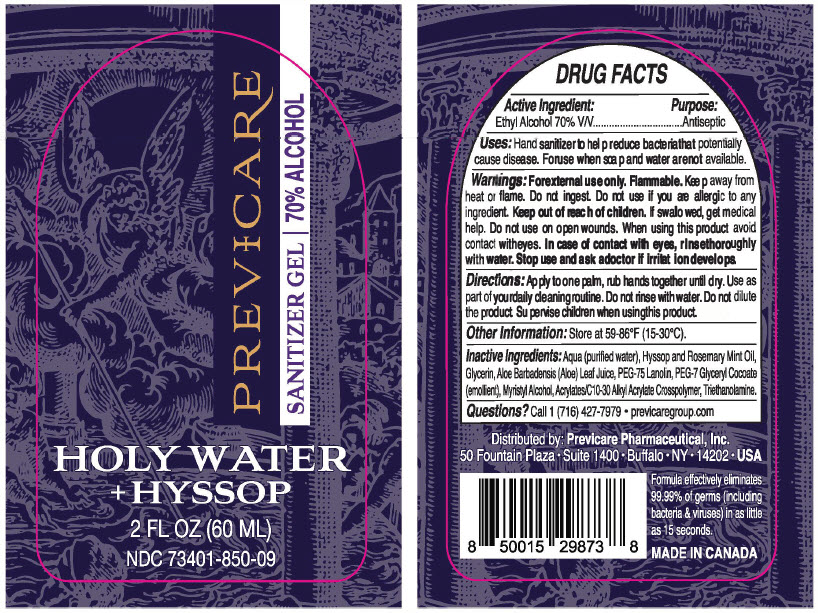 DRUG LABEL: Previcare 
NDC: 73401-849 | Form: GEL
Manufacturer: Previcare Pharmaceutical, Inc.
Category: otc | Type: HUMAN OTC DRUG LABEL
Date: 20210210

ACTIVE INGREDIENTS: Alcohol 70 mL/100 mL
INACTIVE INGREDIENTS: WATER; GLYCERIN; ALOE VERA LEAF; PEG-75 LANOLIN; MYRISTYL ALCOHOL; CARBOMER INTERPOLYMER TYPE A (ALLYL SUCROSE CROSSLINKED); TROLAMINE; PEG-7 GLYCERYL COCOATE; HYSSOP OIL

Previcare Hyssop Sanitizer Gel

Drug Facts

Active Ingredient

Ethyl Alcohol 70% V/V

Purpose

Antiseptic

Uses

Hand sanitizer to help reduce bacteria that potentially cause disease. For use when soap and water are not available.

Warnings

For external use only. Flammable. Keep away from heat or flame. Do not ingest. Do not use if you are allergic to any ingredient.

Keep out of reach of children. If swallowed, get medical help. Do not use on open wounds. When using ths product avoid contact with eyes. In case of contact with eyes, rinse thoroughly with water. Stop use and ask a doctor if irritation develops.

Directions

Apply to one palm, rub hands together until dry. Use as part of your daily cleaning routine. Do not rinse with water. Do not dilute the product. Supervise children when using this product.

Other Information

Store at 50-86°F (15-30°C).

Inactive Ingredients

Aqua (purified water), Hyssop and Rosemary Mint Oil, Glycerin, Aloe Barbadensis (Aloe) Leaf Juice, PEG-75 Lanolin, PEG-7 Glyceryl Cocoate (emollient), Myristyl Alcohol, Acrylates/C10-30 Alkyl Acrylate Crosspolymer, Triethanolamine.

Questions?

Call 1 (716) 427-7979

Distributed by: Previcare Pharmaceutical, Inc.
50 Fountain Plaza • Suite 1400 • Buffalo • NY • 14202 • USA

PRINCIPAL DISPLAY PANEL - 60 ML Bottle Label - NDC 73401-849

PREVICARE
SANITIZER GEL | 70% ALCOHOL

HYSSOP

2 FL OZ (60 ML)

NDC 73401-849-09

PRINCIPAL DISPLAY PANEL - 60 ML Bottle Label - NDC 73401-850

PREVICARE
SANITIZER GEL | 70% ALCOHOL

HOLY WATER
+ HYSSOP

2 FL OZ (60 ML)

NDC 73401-850-09